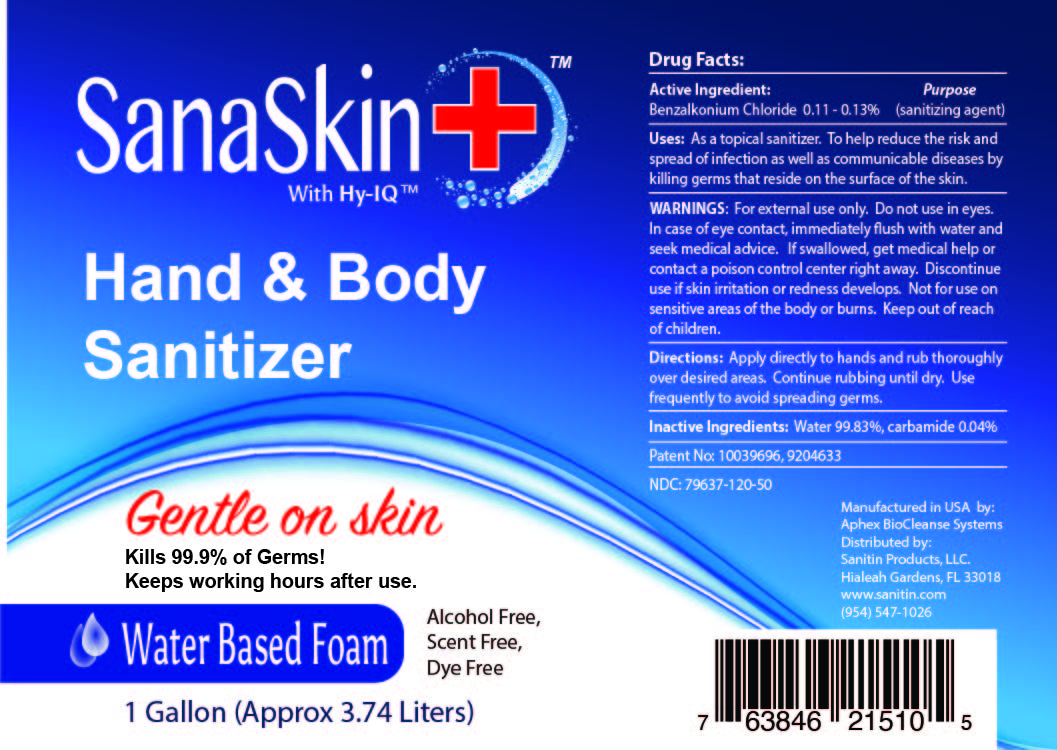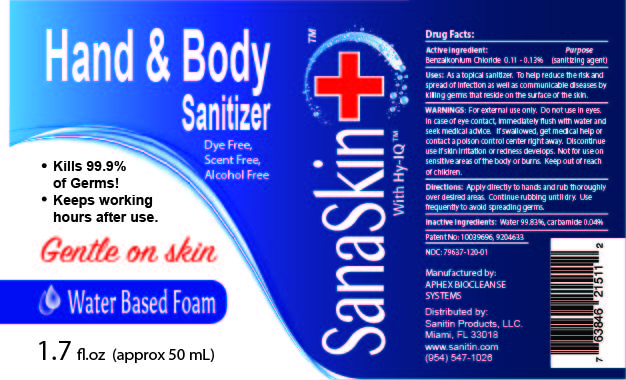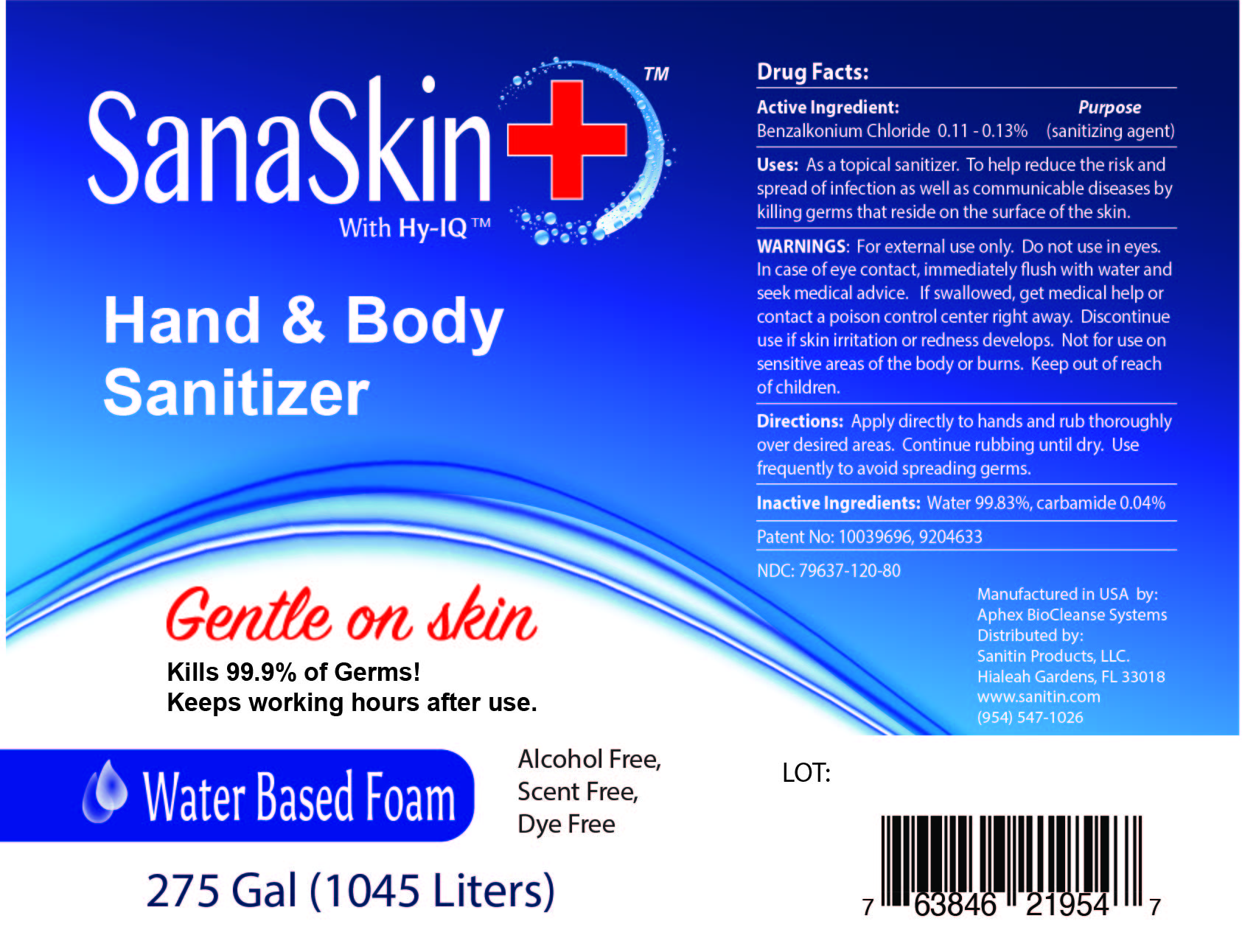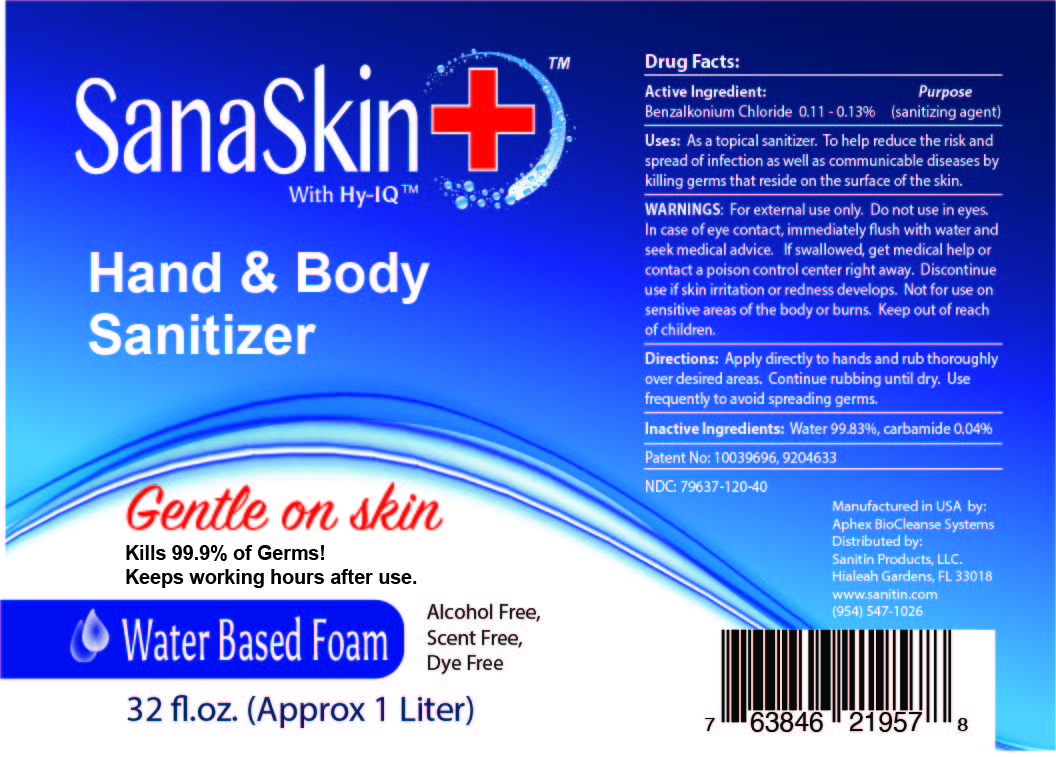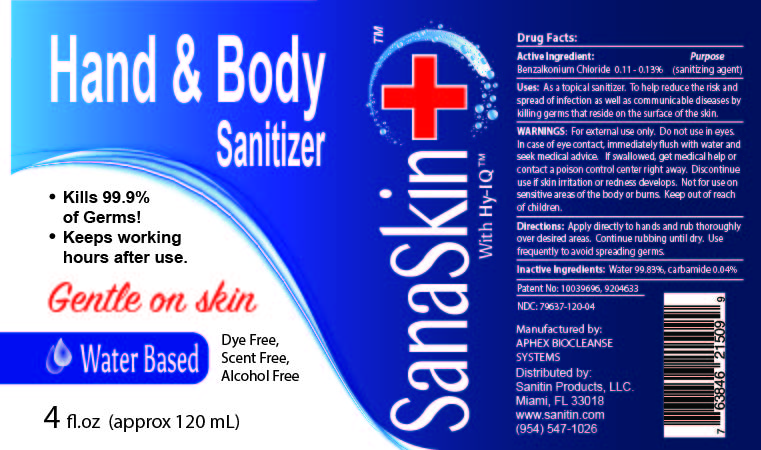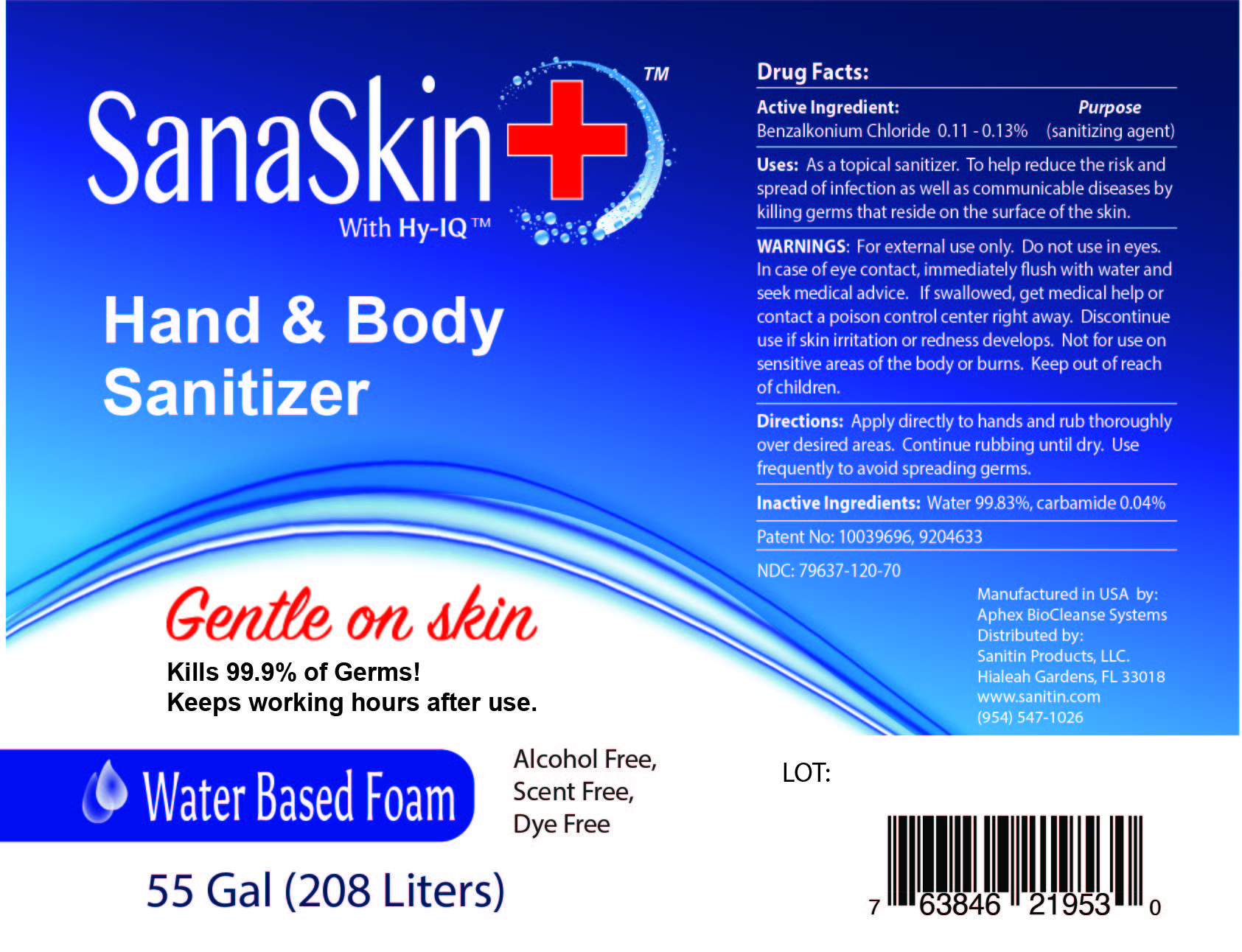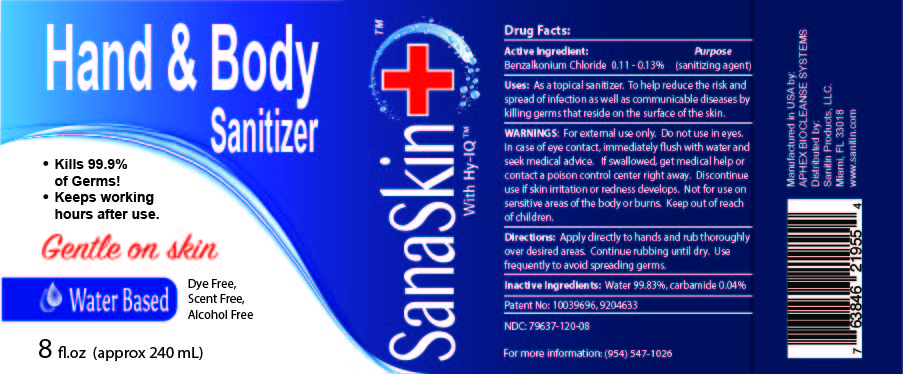 DRUG LABEL: SanaSkin Hand and Body Sanitizer
NDC: 79637-120 | Form: SOLUTION
Manufacturer: Sanitin Products, LLC
Category: otc | Type: HUMAN OTC DRUG LABEL
Date: 20200721

ACTIVE INGREDIENTS: BENZALKONIUM CHLORIDE 0.0013 g/1 mL
INACTIVE INGREDIENTS: UREA; WATER

SanaSkin Sanitizer Hand Sanitizer

Active Ingredient

Benzalkonium chloride 0.11 - 0.13%

Purpose

(sanitizing agent)

Purpose

Sanitizing agent

Directions

Apply directly to hands and rub thoroughly over desired areas. Continue rubbing until dry. Use frequently to avoid spreading germs.

Uses

As a topical sanitizer. To help reduce the risk and spread of infection as well as communicable diseases by killing germs that reside on the surface of the skin.

Warning

For external use only. do not use in eyes. In case of eye contact, immediately flush with water and seek medical advise. If swallowed, get medical help or contact poison control center right away. Discontinue use if skin irritation or redness develops. Not for use on sensitive areas of the body or burns. Keep out of reach of children

Keep out of reach of children

Inactive Ingredients

Inactive ingredients: Water 99.83%, carbamide 0.04%